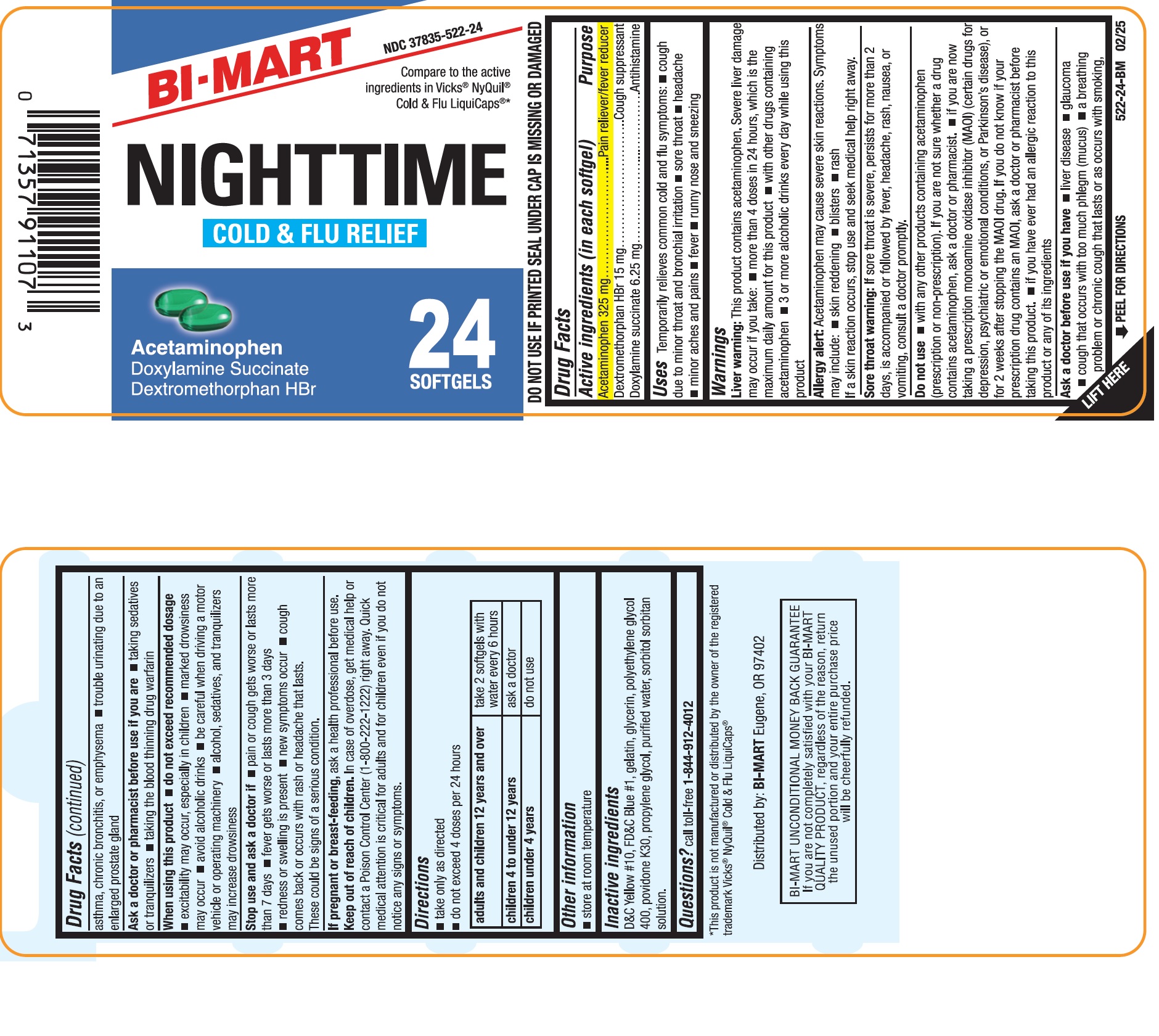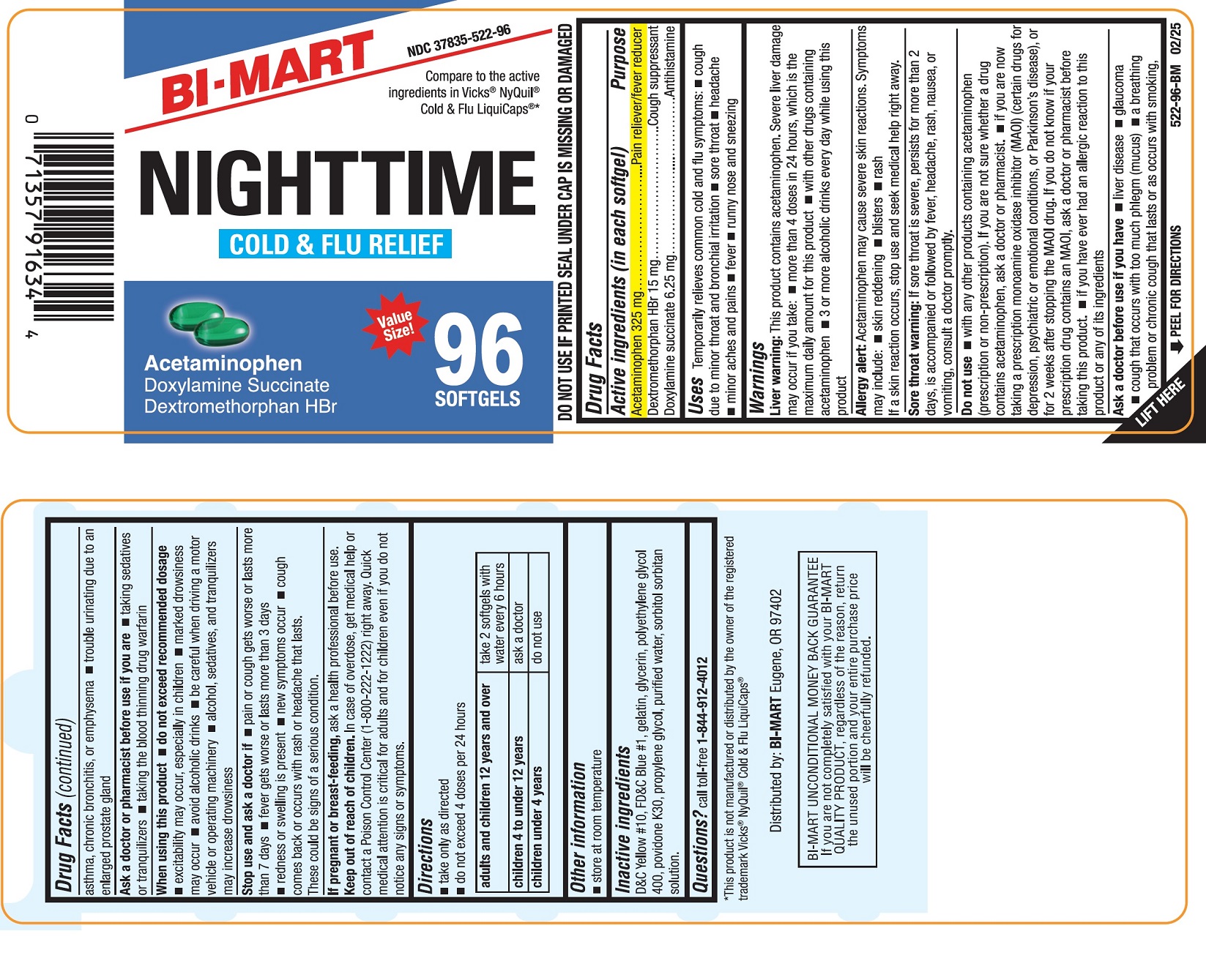 DRUG LABEL: Nighttime Cold and Flu Relief
NDC: 37835-522 | Form: CAPSULE, LIQUID FILLED
Manufacturer: Bi-Mart
Category: otc | Type: HUMAN OTC DRUG LABEL
Date: 20250301

ACTIVE INGREDIENTS: ACETAMINOPHEN 325 mg/1 1; DEXTROMETHORPHAN HYDROBROMIDE 15 mg/1 1; DOXYLAMINE SUCCINATE 6.25 mg/1 1
INACTIVE INGREDIENTS: FD&C BLUE NO. 1; D&C YELLOW NO. 10; GELATIN; GLYCERIN; POLYETHYLENE GLYCOL 400; POVIDONE K30; PROPYLENE GLYCOL; WATER; SORBITOL SOLUTION; SORBITAN

Night-Time Cold & Flu Relief

Active ingredients (in each softgels)

Acetaminophen 325 mg

Dextromethorphan HBr 15 mg

Doxylamine succinate 6.25 mg

Purpose

Pain reliever/fever reducer
Cough suppressant
Antihistamine

Uses

Temporarily relieves common cold and flu symptoms:

- cough due to minor throat and bronchial irritation
- sore throat
- headache
- minor aches and pains
- fever
- runny nose and sneezing

Warnings

Liver warning:This product contains acetaminophen. Severe liver damage may occur if you take

- more than 4 doses in 24 hours, which is the maximum daily amount for this product
- with other drugs containing acetaminophen
- 3 or more alcoholic drinks every day while using this product

Allergy alert:Acetaminophen may cause severe skin reactions. Symptoms may include:

- skin reddening
- blisters
- rash

If a skin reaction occurs, stop use and seek medical help right away.

Sore throat warning:If sore throat is severe, persists for more than 2 days, is accompanied or followed by fever, headache, rash, nausea, or vomiting, consult a doctor promptly.

Do not use

- with any other drug containing acetaminophen (prescription or non-prescription).
- if you are not sure whether a drug contains acetaminophen, ask a doctor or pharmacist.
- if you are now taking a prescription monoamine oxidase inhibitor (MAOI) (certain drugs for depression, psychiatric or emotional conditions, or Parkinson’s disease), or for 2 weeks after stopping the MAOI drug. If you do not know if your prescription drug contains an MAOI, ask a doctor or pharmacist before taking this product.
- if you have ever had an allergic reaction to this product or any of its ingredients

Ask a doctor before use if you have

- liver disease
- glaucoma
- cough that occurs with too much phlegm (mucus)
- a breathing problem or chronic cough that lasts or as occurs with smoking, asthma, chronic bronchitis or emphysema
- trouble urinating due to enlarged prostate gland

Ask a doctor or pharmacist before use if you are

- taking sedatives or tranquilizers
- taking the blood thinning drug warfarin

When using this product

- do not exceed recommended dosage
- excitability may occur, especially in children
- marked drowsiness may occur
- avoid alcoholic drink
- be careful when driving a motor vehicle or operating machinery
- alcohol, sedatives, and tranquilizers may increase drowsiness

Stop use and ask a doctor if

- pain or cough gets worse or lasts more than 7 days
- fever gets worse or lasts more than 3 days
- redness or swelling is present
- new symptoms occur
- cough comes back or occurs with rash or headache that lasts.

These could be signs of a serious condition.

If pregnant or breast-feeding,ask a health professional before use.

Keep out of reach of children

In case of overdose, get medical help or contact a Poison Control Center (1-800-222-122) right away. Quick medical attention is critical for adults and for children even if you do not notice any signs or symptoms.

Direction

- take only as directed
- do not exceed 4 doses per 24 hours

adults and children 12 years and over | take 2 softgels with water every 6 hours
children 4 to under 12 years | ask a doctor
children under 4 years | do not use

Other information

- store at room temperature.
- DO NOT USE IF PRINTED SEAL UNDER CAP IS MISSING OR DAMAGED

Inactive ingredients

D&C yellow# 10, FD&C Blue #1, Gelatin, Glycerin, Polyethylene Glycol 400, Povidone K30, Propylene Glycol, Purified Water, Sorbitol Sorbitan Solution

Questions?

call toll-free 1-844-912-4012

Distributed by:

BI-MART

Eugene, OR 97402

PRINCIPAL DISPLAY PANEL-24 Count

NDC 37835-522-24

Compare to the active ingredients in Vicks®NyQuil®Cold & Flu LiquiCaps®*

NIGHTTIME COLD AND FLU RELIEF

Acetaminophen,

Doxylamine Succinate,

Dextromethorphan HBr

24 SoftGels

*This product is not manufactured or distributed by the owner of the registered trademark Vicks®NyQuil®Cold & Flu LiquiCaps®*

PRINCIPAL DISPLAY PANEL-96 Count

NDC 37835-522-96

Compare to the active ingredients in Vicks®NyQuil®Cold & Flu LiquiCaps®*

NIGHTTIME COLD AND FLU RELIEF

Acetaminophen,

Doxylamine Succinate,

Dextromethorphan HBr

96 SoftGels

*This product is not manufactured or distributed by the owner of the registered trademark Vicks®NyQuil®Cold & Flu LiquiCaps®*